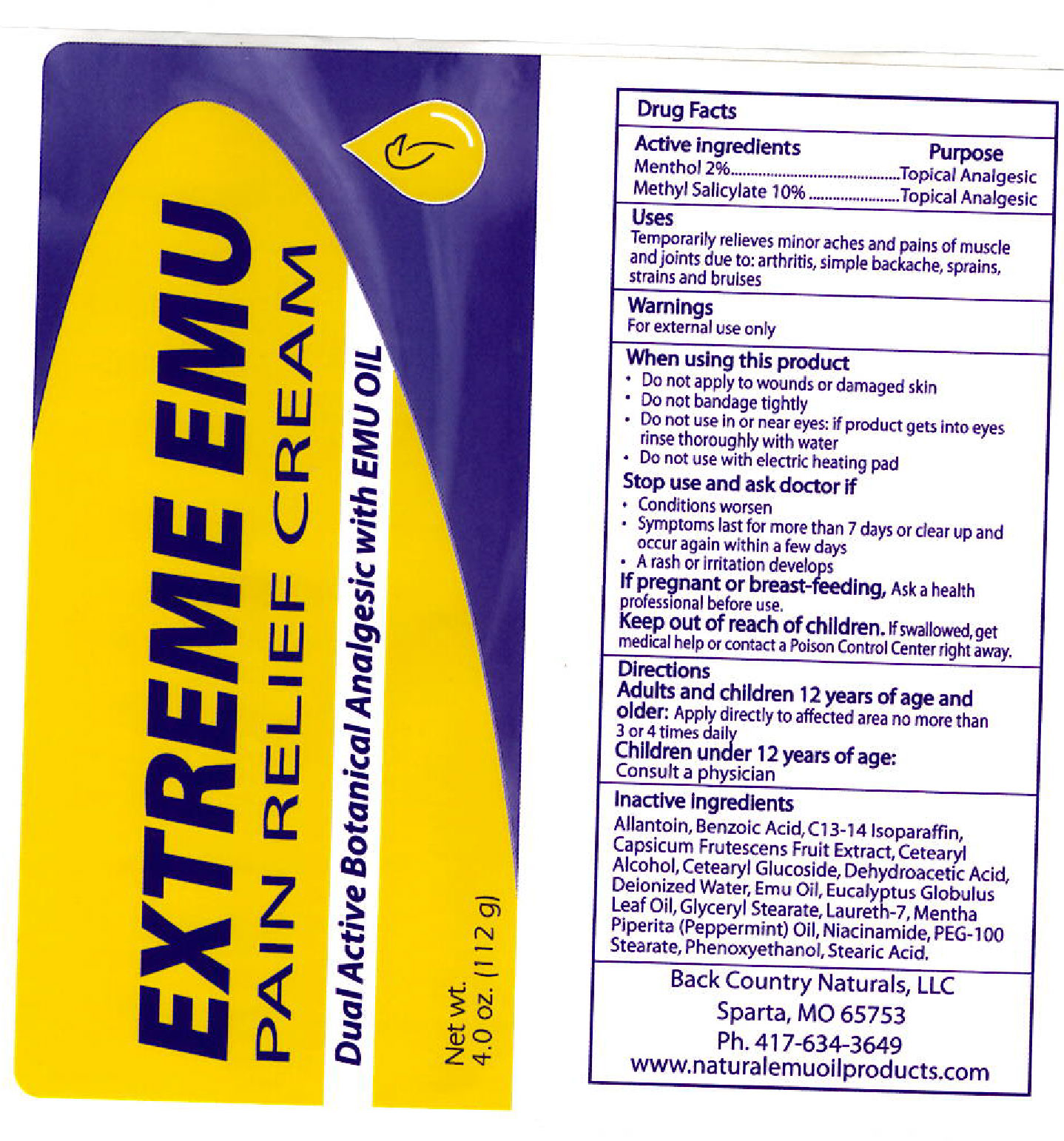 DRUG LABEL: EXTREME EMU
NDC: 76348-495 | Form: CREAM
Manufacturer: Renu Laboratories, LLC
Category: otc | Type: HUMAN OTC DRUG LABEL
Date: 20251114

ACTIVE INGREDIENTS: METHYL SALICYLATE 11.2 g/112 g; MENTHOL 2.24 g/112 g
INACTIVE INGREDIENTS: CETOSTEARYL ALCOHOL; CETEARYL GLUCOSIDE; GLYCERYL MONOSTEARATE; WATER; PEPPERMINT OIL; C13-14 ISOPARAFFIN; DEHYDROACETIC ACID; PEG-100 STEARATE; TABASCO PEPPER; ALLANTOIN; PHENOXYETHANOL; BENZOIC ACID; NIACINAMIDE; LAURETH-7; STEARIC ACID; SODIUM ACRYLOYLDIMETHYLTAURATE-ACRYLAMIDE COPOLYMER (1:1; 90000-150000 MPA.S); EMU OIL; EUCALYPTUS OIL

EXTREME EMU

ACTIVE INGREDIENTS

Menthol 2%

Methyl Salicylate 10%

PURPOSE

Topical Analgesic

Topical Analgesic

USES

Temporarily relieves minor aches and pains of muscle and joints due to: arthritis, simple backache, sprains, strains and bruises

Warnings

For external use only

When using this product

- Do not apply to wounds or damaged skin
- Do not bandage tightly
- Do not use in or near eyes; if product gets into eyes rinse thoroughly with water
- Do not use with an electric heating pad

Stop use and ask doctor if

- Conditions worsen
- Symptoms last for more than 7 days or clear up and occur again within a few days
- A rash or irritation develops

If pregnant or breast-feeding,

Ask a health professional before use.

Keep out of reach of children.

If swallowed, get medical help or contact a Poison Control Center right away.

Inactive Ingredients

Allantoin, Benzoic Acid, C13-14 Isoparaffin, Capsicum Frutescens Fruit Extract, Cetearyl Alcohol, Cetearyl Glucoside, Dehydroacetic Acid, Deionized Water, Emu Oil, Eucalyptus Globulus Leaf Oil, Glyceryl Stearate, Laureth-7, Mentha Piperita (Peppermint) Oil, Niacinamide, PEG-100 Stearate, Phenoxyethanol, Stearic Acid.

EXTREME EMU

Dual Active Botanical Analgesic with EMU OIL

QUESTIONS

Manufactured by:

Renu Labs Inc.

Ivyland, PA 18974

www.RenuLabs.com

Directions

Adults and children 12 years of age and

older: Apply directly to affected area no more than 3 to 4 times daily.

EXTREME EMU

TUBE LABEL ART FOR EXTREME EMU